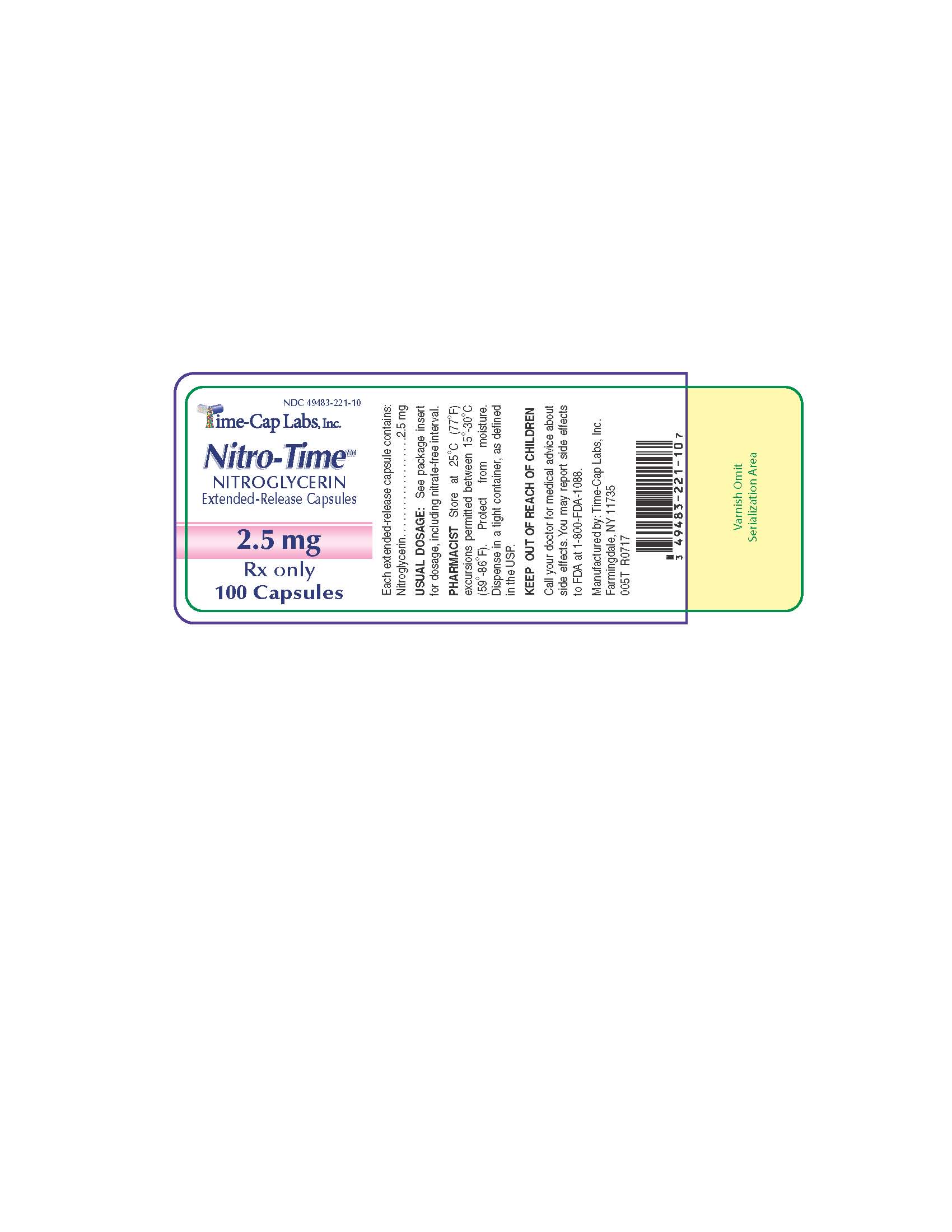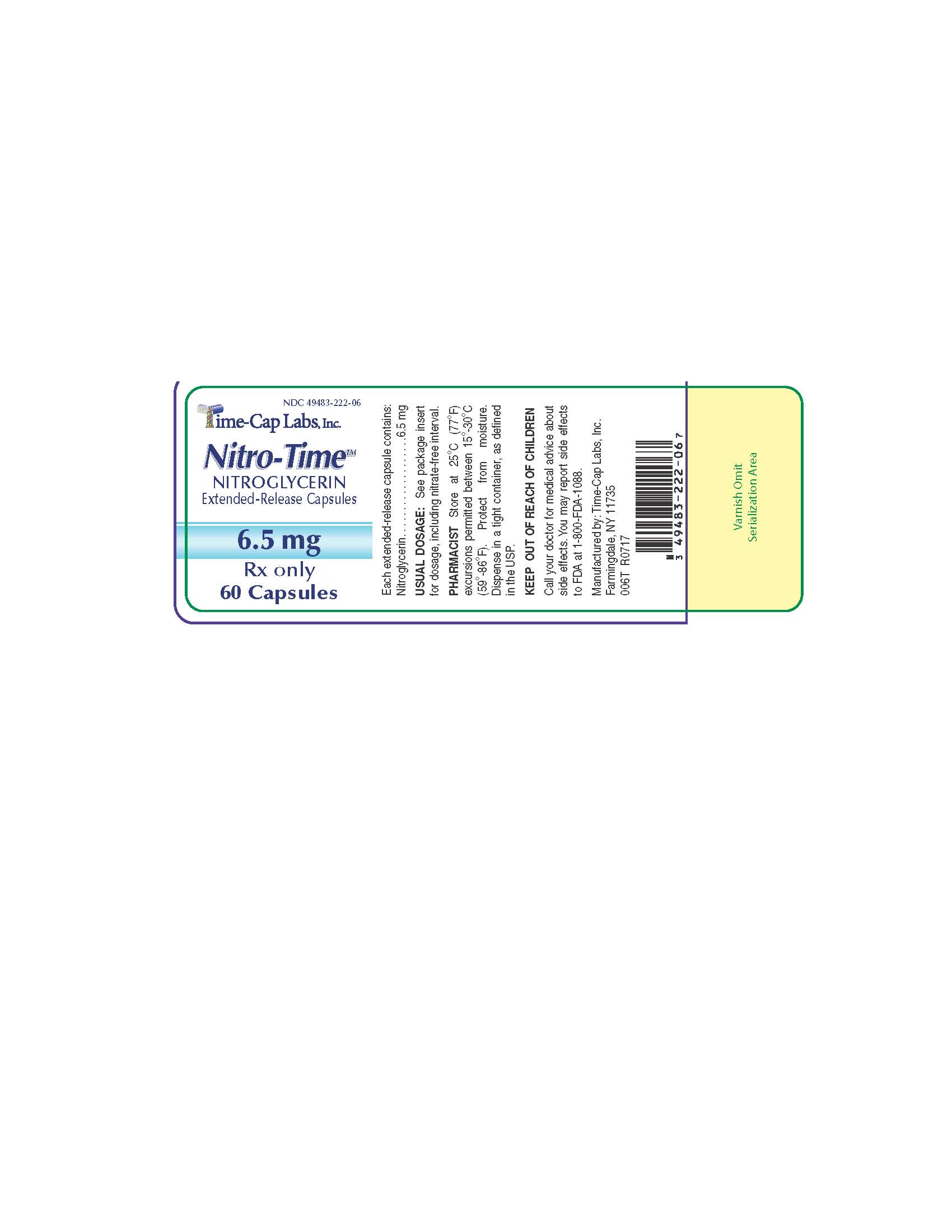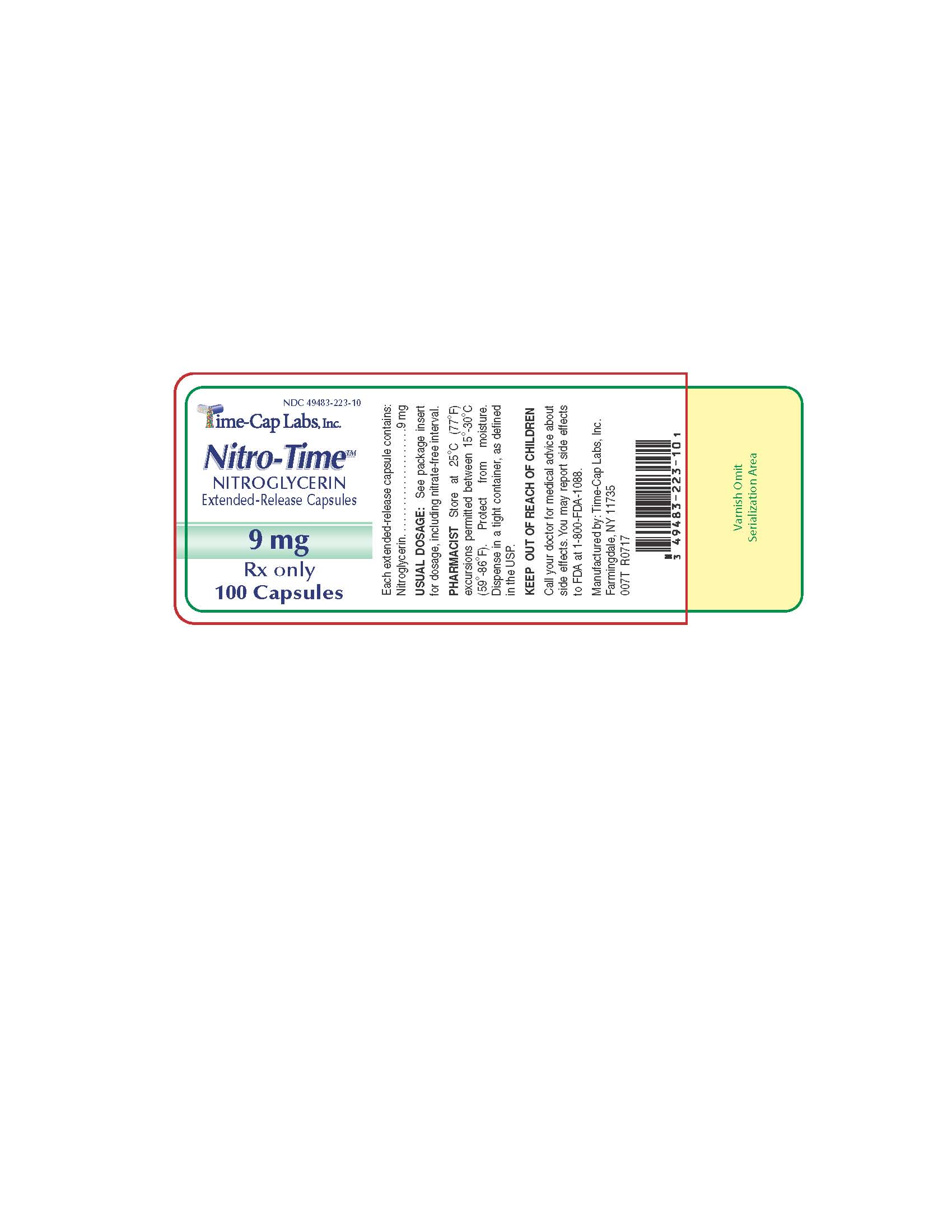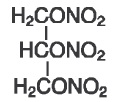 DRUG LABEL: NITRO-TIME
NDC: 49483-221 | Form: CAPSULE
Manufacturer: TIME CAP LABORATORIES, INC
Category: prescription | Type: HUMAN PRESCRIPTION DRUG LABEL
Date: 20251119

ACTIVE INGREDIENTS: NITROGLYCERIN 2.5 mg/1 1
INACTIVE INGREDIENTS: D&C YELLOW NO. 10; STARCH, CORN; ETHYLCELLULOSES; FD&C BLUE NO. 1; FD&C BLUE NO. 2; FD&C RED NO. 40; GELATIN; FERROSOFERRIC OXIDE; LACTOSE MONOHYDRATE; PROPYLENE GLYCOL; SHELLAC; SUCROSE; TALC; WHITE WAX; D&C RED NO. 28

NITROGLYCERIN 2.5 MG, 6.5 MG and 9.0 MG

DESCRIPTION

Nitroglycerin is 1,2,3-propanetriol trinitrate, an organic nitrate whose structural formula is:

Molecular Formula: C3H5N3O9

Molecular Weight: 227.09

The organic nitrates are vasodilators, active on both arteries and veins. Each Extended-Release Capsule, for oral administration contains 2.5 mg, 6.5 mg or 9 mg of Nitroglycerin.

The inactive ingredients in each capsule are corn starch, ethylcellulose, gelatin, lactose

monohydrate, propylene glycol, shellac, sugar, talc, and wax. Additionally, the 2.5 mg capsule contains D&C Red #28, D&C Yellow #10, D&C Yellow #10 Aluminum Lake, FD&C Blue #1, FD&C Blue #1 Aluminum Lake, FD&C Blue #2 Aluminum Lake, FD&C Red #40, FD&C Red #40 Aluminum Lake, Iron Oxide Black; the 6.5 mg capsule contains D&C Red #33, D&C Yellow #10, FD&C Blue #1, FD&C Yellow #6, Simethicone, Titanium Dioxide; the 9 mg capsule contains D&C Yellow #10, D&C Yellow #10 Aluminum Lake, FD&C Blue #1 Aluminum Lake, FD&C Blue #2 Aluminum Lake, FD&C Green #3, FD&C Red #40 Aluminum Lake, FD&C Yellow #6, Iron Oxide Black, Titanium Dioxide.

CLINICAL PHARMACOLOGY

CLINICAL PHARMACOLOGY: The principal pharmacological action of nitroglycerin is relaxation of vascular smooth muscle and consequent dilation of peripheral arteries and veins, especially the latter. Dilatation of the veins promotes peripheral pooling of blood and decreases venous return to the heart, thereby reducing left ventricular end-diastolic pressure and pulmonary capillary wedge pressure (preload). Arteriolar relaxation reduces systemic vascular resistance, systolic arterial pressure, and mean arterial pressure (afterload). Dilatation of the coronary arteries also occurs. The relative importance of preload reduction, afterload reduction, and coronary dilatation remains undefined.

Dosing regimens for most chronically used drugs are designed to provide plasma concentrations that are continuously greater than minimally effective concentration. This strategy is inappropriate for organic nitrates. Several well-controlled clinical trials have used exercise testing to assess the anti-anginal efficacy of continuously-delivered nitrates. In the large majority of these trials, active agents were indistinguishable from placebo after 24 hours (or less) of continuous therapy. Attempts to overcome nitrate tolerance by dose escalation, even to doses far in excess of those used acutely, have consistently failed. Only after nitrates had been absent from the body for several hours was their anti-anginal efficacy restored.

PHARMACOKINETICS

Pharmacokinetics: The volume of distribution of nitroglycerin is about 3 L/kg, and nitroglycerin, is cleared from this volume at extremely rapid rates, with a resulting serum half-life of about 3 minutes. The observed clearance rates (close to 1 L/kg/min) greatly exceed hepatic blood flow; known sites of extrahepatic metabolism include red blood cells and vascular walls.

The first products in the metabolism of nitroglycerin are inorganic nitrate and the 1,2- and 1,3-dinitroglycerols. The dinitrates are less effective vasodilators than nitroglycerin, but they are longer-lived in the serum, and their net contribution to the overall effect of chronic nitroglycerin regimens is not known. The dinitrates are further metabolized to (non-vasoactive) mononitrates and, ultimately, to glycerol and carbon dioxide.

To avoid development of tolerance to nitroglycerin, drug-free intervals of 10 - 12 hours are known to be sufficient; shorter intervals have not been well studied. In one well controlled clinical trial, subjects receiving nitroglycerin appeared to exhibit a rebound or withdrawal effect, so that their exercise tolerance at the end of the daily drug-free interval was less than that exhibited by the parallel group receiving placebo.

Reliable assay techniques for plasma nitroglycerin levels have only recently become available, and studies using these techniques to define the pharmacokinetics of oral nitroglycerin preparations have not been reported. Published studies using older techniques provide results that often differ, in similar experimental settings, by an order of magnitude.

CLINICAL TRIALS EXPERIENCE

Clinical trials: Controlled trials of single oral doses of nitroglycerin have demonstrated that nitroglycerin capsules can effectively reduce exercise-related angina for up to 5 hours. Anti-anginal activity is present about 1 hour after ingestion of a capsule.

Controlled trials of multiple-dose oral nitroglycerin have shown statistically significant anti-anginal efficacy 2 1/2 and 4 hours after a dose when oral nitroglycerin had been administered four times a day for 2 weeks or three times a day for 1 week. As noted above, careful studies with other formulations of nitroglycerin have shown that maintenance of continuous 24-hour plasma levels of nitroglycerin results in insurmountable intolerance.

Presumably, the studied 1-week and 2-week regimens of oral nitroglycerin therapy achieved adequate nitrate-free intervals by non-uniformity of dosing interval, with longer intervals overnight. The investigators did not report how subjects interpreted their dosing instruction, and they similarly did not report which dose of the day was the one after which they obtained the end-of trial exercise results.

Thus, these studies of oral nitroglycerin should not be interpreted as demonstrations that these regimens provide round-the-clock anti-anginal protection. From large, well-controlled studies of other nitroglycerin formulations, it is reasonable to believer that the maximal achievable daily duration of anti-anginal effect from Nitroglycerin Extended-Release Capsules is about 12 hours.

In some controlled trials of other organic nitrate formulations, efficacy has declined with time. Because the controlled, multiple-dose trails of oral nitroglycerin did not include exercise tests before the last day of treatment, it is not known how the efficacy of Nitroglycerin Extended-Release Capsules may vary during extended therapy.

INDICATIONS AND USAGE: Nitroglycerin Extended-Release Capsules are indicated for the prevention of angina pectoris due to coronary artery disease. The onset of action of oral nitroglycerin is not sufficiently rapid for this product to be useful in aborting an acute anginal episode.

CONTRAINDICATIONS

CONTRAINDICATIONS: Allergic reactions to organic nitrates are extremely rare, but they do occur. Nitroglycerin is contraindicated in patients who are allergic to it.

WARNINGS AND PRECAUTIONS

WARNINGS: Amplification of the vasodilatory effects of nitroglycerin by sildenafil can result in severe hypotension. The time course and dose dependence of this interaction have not been studied. Appropriate supportive care has not been studied, but it seems reasonable to treat this as a nitrate overdose, with elevation of the extremities and with central volume expansion.

The benefits of oral nitroglycerin in patients with acute myocardial infarction or congestive heart failure have not been established. If one elects to use nitroglycerin in these conditions, careful clinical or hemodynamic monitoring must be used to avoid the hazards of hypotension and tachycardia.

Because the effects at capsules are so difficult to terminate rapidly, that are not recommended in these settings.

PRECAUTIONS:

General: Severe hypotension, particularly with upright posture, may occur with even small doses of nitroglycerin. This drug should therefore be used with caution in patients who may be volume depleted or who, for whatever reason, are already hypotensive. Hypotension induced by nitroglycerin may be accompanied by paradoxical bradycardia and increased angina pectoris.

Nitrate therapy may aggravate the angina caused by hypertrophic cardiomyopathy.

As tolerance in other forms of nitroglycerin develops, the effect of sublingual nitroglycerin on exercise tolerance, although still observable, is somewhat blunted. In industrial workers who have had long-term exposure to unknown (presumably high) doses of organic nitrates, tolerance clearly occurs. Chest pain, acute myocardial infarction, and even sudden death have occurred during temporary withdrawal of nitrates from these workers, demonstrating the existence of true physical dependence.

Some clinical trials in angina patients have provided nitroglycerin for about 12 continuous hours of every 24-hour day. During the nitrate-free intervals in some of these trials, anginal attacks have been more easily provoked than before treatment, and patients have demonstrated hemodynamic rebound and decreased exercise tolerance. The importance of these observations to the routine, clinical use at oral nitroglycerin is not known.

PATIENT COUNSELING INFORMATION

Information for Patients: Daily headaches sometimes accompany treatment with nitroglycerin. In patients who get these headaches, the headaches are a marker of the activity of the drug. Patients should resist the temptation to avoid headaches by altering the schedule of their treatment with nitroglycerin, since loss of headache is likely to be associated with simultaneous loss of anti-anginal efficacy.

Treatment with nitroglycerin may be associated with lightheadedness on standing, especially just after rising from a recumbent or seated position. This effect may be more frequent in patients who have also consumed alcohol. Patient instruction leaflet is included.

DRUG INTERACTIONS

Drug interactions: The vasodilating effects of nitroglycerin may be additive with those of other vasodilators. Alcohol, in particular, has been found to exhibit additive effects of this variety.

Marked symptomatic orthostatic hypotension has been reported when calcium channel blockers and organic nitrates were used in combination. Dose adjustments of either class of agents may be necessary.

CARCINOGENESIS AND MUTAGENESIS AND IMPAIRMENT OF FERTILITY

Carcinogenesis, Mutagenesis, and Impairment of Fertility: Studies to evaluate the carcinogenic or mutagenic potential of nitroglycerin have not been performed. Nitroglycerin’s effect upon reproductive capacity is similarly unknown.

PREGNANCY

Pregnancy Category C: Animal reproduction studies have not been conducted with nitroglycerin. It is also not known whether nitroglycerin can cause fetal harm when administered to a pregnant woman or whether it can affect reproductive capacity. Nitroglycerin should be given to a pregnant women only if clearly needed.

NURSING MOTHERS

Nursing Mothers: It is not known whether nitroglycerin is excreted in human milk. Because many drugs are excreted in human milk, caution should be exercised when nitroglycerin is administered to a nursing woman.

PEDIATRIC USE

Pediatric Use: Safety and effectiveness in children have not been established.

GERIATRIC USE

Geriatic Use: Clinical studies of Nitroglycerin Extended-Release Capsules did not include sufficient numbers of subjects aged 65 and over to determine whether they respond differently from younger subjects. Other reported clinical experience has not identified differences in responses between the elderly and younger patients. In general, dose selection for an elderly patient should be cautious, usually starting at the low end of the dosing range, reflecting the greater frequency of decreased hepatic, renal, or cardiac function, and of concomitant disease or other drug therapy.

ADVERSE REACTIONS

ADVERSE REACTIONS: Adverse reactions to nitroglycerin are generally dose-related, and almost all of these reactions are the result of nitroglycerin's activity as a vasodilator. Headache, which may be severe, is the most commonly reported side effect. Headache may be recurrent with each daily dose, especially at higher doses. Transient episodes of lightheadedness, occasionally related to blood pressure changes, may also occur. Hypotension occurs infrequently, but in some patients may be severe enough to warrant discontinuation of therapy. Syncope, crescendo angina, and rebound hypertension have been reported but are uncommon.

Allergic reactions to nitroglycerin are also uncommon, and the great majority of those reported have been cases of contact dermatitis or fixed drug eruptions in patients receiving nitroglycerin in ointments or patches. There have been a few reports of genuine anaphylactoid reactions, and these reactions can probably occur in patients receiving nitroglycerin by any route.

Extremely rarely, ordinary doses of organic nitrates have caused methemoglobinemia in normal seeming patients; for further discussion of its diagnosis and treatment see OVERDOSAGE.

Data are not available to allow estimation of the frequency of adverse reactions during treatment with Nitroglycerin Extended-Release Capsules.

OVERDOSAGE

Hemodynamic Effects: The ill effects of nitroglycerin overdose are generally the results of nitroglycerin's capacity to induce vasodilation, venous pooling, reduced cardiac output, and hypotension. These hemodynamic changes may have protean manifestations, including increased intracranial pressure, with any or all of persistent throbbing headache, confusion, and moderate fever; vertigo; palpitations; visual disturbances; nausea and vomiting (possibly with colic and even bloody diarrhea); syncope (especially in the upright posture; air hunger and dyspnea, later followed by reduced ventilatory effort; diaphoresis, with the skin either flushed or cold and clammy; heart block and bradycardia; paralysis; coma; seizures; and death.

Laboratory determinations of serum levels of nitroglycerin and its metabolites are not widely available, and such determinations have, in any event, no established role in the management of nitroglycerin overdose.

No data are available to suggest physiological maneuvers (e.g., maneuvers to change the pH of the urine) that might accelerate elimination of nitroglycerin and its active metabolites. Similarly, it is not known which -if any- of these substances can usefully be removed from the body by hemodialysis.

No specific antagonist to the vasodilator effects of nitroglycerin is known, and no intervention has been the subject of controlled study as a therapy of nitroglycerin overdose. Because the hypotension associated with nitroglycerin overdose is the result of venodilation and arterial hypovolemia, prudent therapy in this situation should be directed toward increase in central fluid volume. Passive elevation of the patient's legs may be sufficient, but intravenous infusion of normal saline or similar fluid may also be necessary.

The use of epinephrine or other arterial vasoconstrictors in this setting is likely to do more harm than good.

In patients with renal disease or congestive heart failure, therapy resulting in central volume expansion is not without hazard. Treatment of nitroglycerin overdose in these patients may be subtle and difficult, and Invasive monitoring may be required.

Methemoglobinemia: Nitrate ions liberated during metabolism of nitroglycerin can oxidize hemoglobin into methemoglobin. Even in patients totally without cytochrome b5 reductase activity, however, and even assuming that the nitrate moieties of nitroglycerin are quantitatively applied to oxidation of hemoglobin, about 1mg/kg of nitroglycerin should be required before any of these patients manifests clinically significant (≥10%) methemoglobinemia. In patients with normal reductase function, significant production of methemoglobin should require even larger doses of nitroglycerin. In one study in which 36 patients received 2-4 weeks of continuous nitroglycerin therapy at 3.1 to 4.4 mg/hr, the average methemoglobin level measured 0.2%; this was comparable to that observed in parallel patients who received placebo.

Not withstanding these observations, there are case reports of significant methemoglobinemia in association with moderate overdoses of organic nitrates. None of the affected patients had been thought to be unusually susceptible. Methemoglobin levels are available from most clinical laboratories. The diagnosis should be suspected in patients who exhibit signs of impaired oxygen delivery despite adequate cardiac output and adequate arterial pO2. Classically, methemoglobinemic blood is described as chocolate brown, without color change on exposure to air.

When methemoglobinemia is diagnosed, the treatment of choice is methylene blue, 1 to 2 mg/kg intravenously.

DOSAGE AND ADMINISTRATION: As noted above (CLINICAL PHARMACOLOGY), careful studies with other formulations of nitroglycerin have shown that maintenance of continuous 24-hour plasma levels of nitroglycerin result in tolerance (i.e. loss of clinical response). Every dosing regimen for Nitroglycerin Extended-Release Capsules should provide a daily nitrate-free interval avoid the development of this tolerance. The minimum necessary length of such an interval has not been defined, but studies with other nitroglycerin formulations have shown that 10-12 hours is sufficient. Large controlled studies with other formulations of nitroglycerin show that no dosing regimen with Nitroglycerin Extended-Release should be expected to provide more than about 12 hours of continuous anti-anginal efficacy per day.

The pharmacokinetics of Nitroglycerin Capsules and the clinical effects of multiple-dose regimens, have not been well studied. In clinical trials, the initial regimen of nitroglycerin has been 2.5 to 6.5 mg three to four times a day, with subsequent upward dose adjustment guided by symptoms and side effects. In one trial, 5 of the 18 subjects were titrated up to a dose of 26 mg four times a day.

HOW SUPPLIED:

Nitroglycerin Extended-Release Capsules, 2.5 mg (Pink and Clear, imprinted TCL 1221) in 60 and 100 count bottles.

HOW SUPPLIED

Nitroglycerin Extended- Release Capsules, 6.5 mg (Blue and Yellow, imprinted TCL 1222) in 60 and 100 count bottles.

HOW SUPPLIED

Nitroglycerin Extended-Release Capsules, 9 mg (Green and Yellow, imprinted TCL 1223) in 60 and 100 count bottles.

Rx only

STORAGE AND HANDLING

STORAGE: Store at controlled room temperature 25 °C (77 °F), excursions permitted between 15°-30 °C (59°-86 °F). Protect from moisture. Dispense in a tight container, as defined in the USP.

Manufactured by:

Time-Cap Labs, Inc.

Farmingdale, NY 11735

Revised November 2025